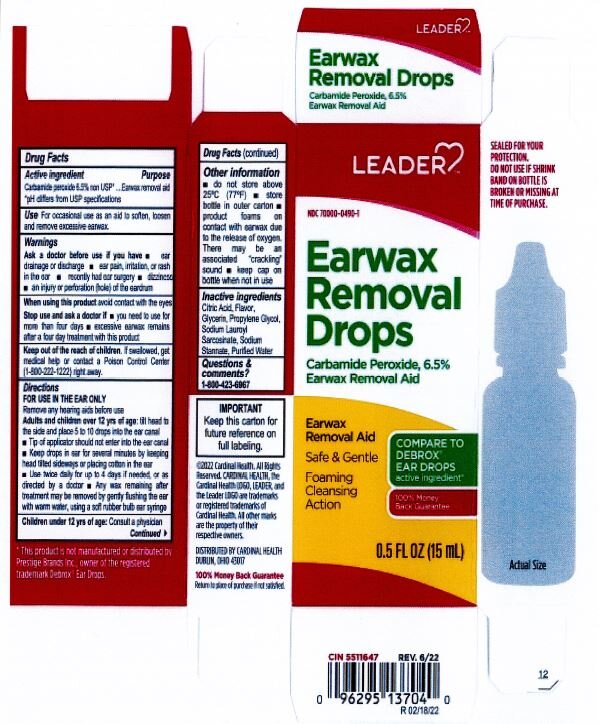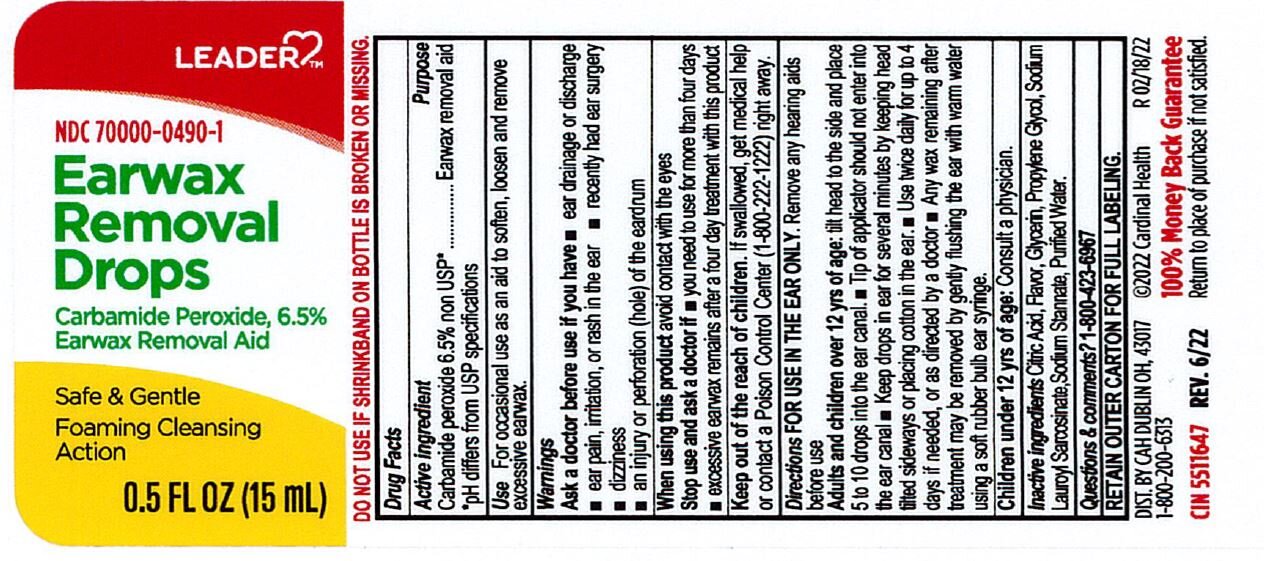 DRUG LABEL: LEADER Earwax Removal Kit
NDC: 70000-0490 | Form: LIQUID
Manufacturer: Cardinal Health, 110 dba Leader
Category: otc | Type: HUMAN OTC DRUG LABEL
Date: 20250728

ACTIVE INGREDIENTS: CARBAMIDE PEROXIDE 6.5 g/100 mL
INACTIVE INGREDIENTS: SODIUM LAUROYL SARCOSINATE; WATER; ANHYDROUS CITRIC ACID; SODIUM STANNATE; GLYCERIN; PROPYLENE GLYCOL

LEADER Earwax Removal Kit

ACTIVE INGREDIENT

Carbamide Peroxide 6.5% non USP*

*pH differs from USP specifications

PURPOSE

Earwax removal aid

INDICATIONS AND USAGE

For occasional use as an aid to soften, loosen, and remove excessive earwax.

Ask a doctor before use if you have:

ear drainage or discharge

ear pain, irritation, or rash in ear

recently had ear surgery

dizziness

an injury or perforation of the eardrum

INACTIVE INGREDIENT

Citric acid

Flavor

Glyrcerin

Propylene glycol

Sodium Lauroyl Sarcosinate

Sodium Stannate

Purified water

DOSAGE AND ADMINISTRATION

- tilt head sideways
- palce 5 to 10 drops into ear
- tip of applicator should not enter ear canal
- keep drops in ear for several minutes by keeping head tilted or placing cotton in the ear
- use twice daily for up to four days if needed, or as directed by a doctor
- any wax remaining after treatment may be removed by gently flushing ear with warm water, using a soft rubber bulb ear syringe

KEEP OUT OF REACH OF CHILDREN

If swallowed, get medical help or contact a Posion Control Center right away.